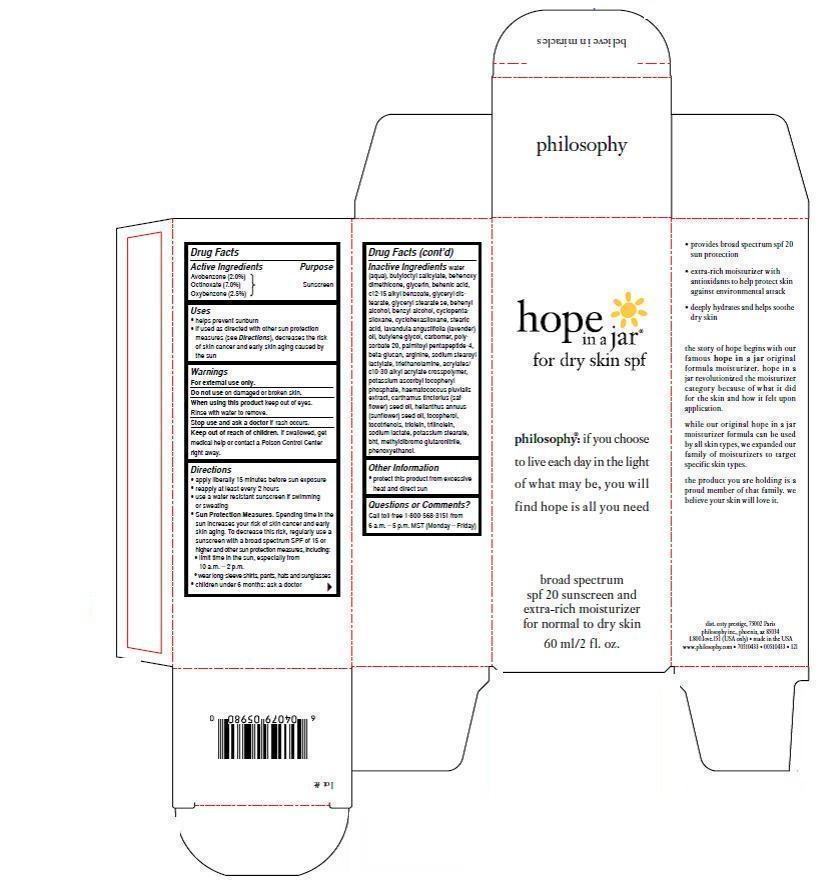 DRUG LABEL: Hope In A Jar For Dry Skin SPF 
NDC: 50184-6400 | Form: CREAM
Manufacturer: Philosophy, Inc.
Category: otc | Type: HUMAN OTC DRUG LABEL
Date: 20130708

ACTIVE INGREDIENTS: Avobenzone 1.392 g/60 mL; Octinoxate 4.242 g/60 mL; Oxybenzone 1.98 g/60 mL
INACTIVE INGREDIENTS: WATER; BUTYLOCTYL SALICYLATE ; DIMETHICONE; GLYCERYL MONOSTEARATE; DOCOSANOIC ACID ; GLYCERIN; C12-15 ALKYL BENZOATE; DOCOSANOL; BENZYL ALCOHOL; CYCLOMETHICONE 6; CYCLOMETHICONE 5; STEARIC ACID; ENGLISH LAVENDER OIL; 1,3-BUTYLENE GLYCOL; CARBOMER 934; POLYSORBATE 20; ARGININE; SODIUM STEAROYL LACTYLATE; TROLAMINE; CARBOMER COPOLYMER TYPE A ; SAFFLOWER OIL; ALPHA-TOCOPHEROL; SQUALENE; RICE BRAN; METHYLDIBROMO GLUTARONITRILE; PHENOXYETHANOL

DRUG FACTS

Active Ingredients

Avobenzone (2.0%)......Sunscreen

Octinoxate (7.0%)........Sunscreen

Ozybenzone (2.5%)......Sunscreen

Purpose

Sunscreen

Uses

- helps prevent sunburn
- if used as directed with other sun protection measures (see Directions), decreases the risk of skin cancer and early skin aging caused by the sun

Warnings

For external use only.

Do not use on damaged or broken skin.

When using this product keep our of eyes.

Rinse with water to remove.

Stop use and ask a doctor if a rash occurs.

Directions

- apply liberally 15 minutes before sun exposure
- reapply at least every 2 hours
- use a water resistant sunscreen if swimming or sweating
- Sun Protection Measures. Spending time in the sun increases your risk of skin cancer and early skin aging. To decrease this risk, regularly use a sunscreen with a broad spectrum SPF of 15 or higher and other sun protection measures, including:
- limit time in the sun, especially from 10 a.m.-2 p.m.
- wear long-sleeve shirts, pants, hats and sunglasses
- children under 6 months: ask a doctor

Keep out of reach of children. If swallowed, get medical help or contact a Poison Control Center right away.

Other Information

- protect this product from excessive heat and direct sun

Questions or Comments?

Call toll-free 1-800-568-3151 from 6 a.m.-5 p.m. MST (Monday-Friday)

Inactive Ingredients

Water (aqua), butyloctyl salicylate, behenoxy dimethicone, glycerin, behinic acid, c12-c14 alkyl benzoate, glyceryl distearate, blyceryl stearate se, behenyl alcohol, benzyl alcohol, cyclopentasiloxane, cyclohexasiloxane, stearic acid, lavandula angustifolia (lavender) oil, butylene glycol, carbomer, polysorbate 20, palmitoyl pentapeptide-4, beta-glucan, arginine, sodium stearoyl lactylate, triethanolamine, acrylate/c10-30 alkyl acrylate crosspolymer, potassium ascorbyl tocopheryl phosphate, haematococcus pluvialis extract, carthamus tinctorius (safflower) seed oil, helianthus annus (sunflower) seed oil, tocopherol, tocotrienols, trilein, trilinolein, sodium lactate, potassium stearate, bht, mthyldibromo glutaronitrile, phenoxyethanol.